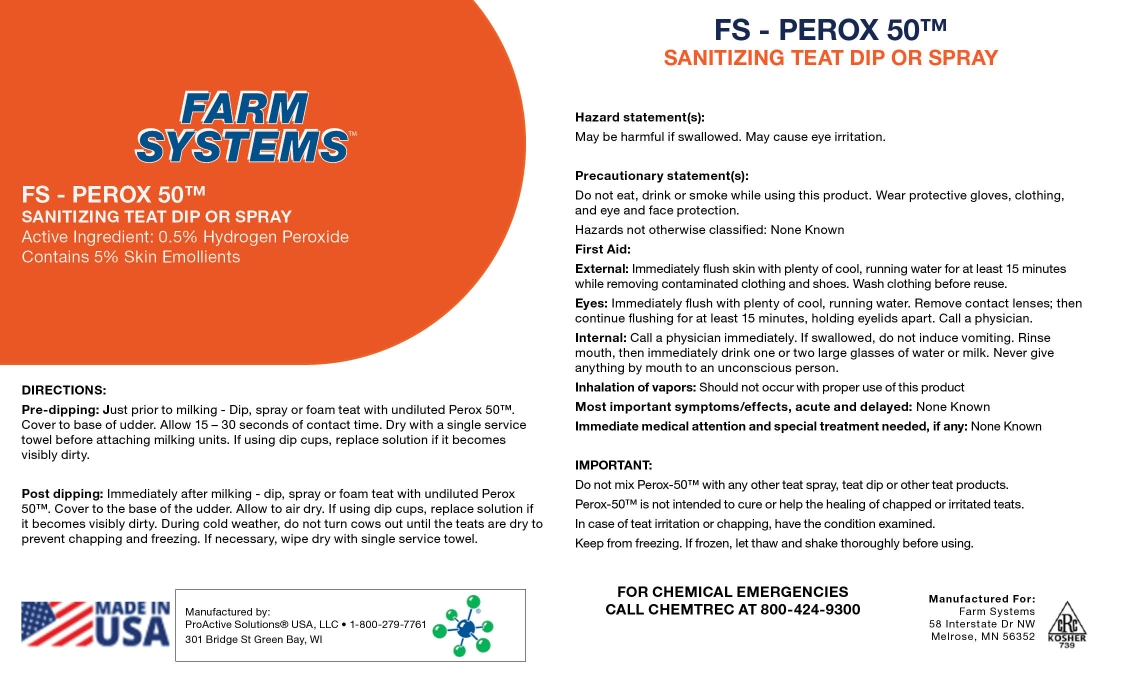 DRUG LABEL: FS Perox 50
NDC: 86193-4672 | Form: LIQUID
Manufacturer: Genex Cooperative, Inc.
Category: animal | Type: OTC ANIMAL DRUG LABEL
Date: 20240404

ACTIVE INGREDIENTS: HYDROGEN PEROXIDE 0.5 kg/100 kg

FS Perox 50

FS Perox 50

Hazard statement(s):
May be harmful if swallowed. May cause eye irritation.
Precautionary statement(s):
Do not eat, drink or smoke while using this product. Wear protective gloves, clothing, and eye and face protection.
Hazards not otherwise classified: None Known
First Aid:
External: Immediately flush skin with plenty of cool, running water for at least 15 minutes while removing contaminated clothing and shoes. Wash clothing before reuse.
Eyes: Immediately flush with plenty of cool, running water. Remove contact lenses; then continue flushing for at least 15 minutes, holding eyelids apart. Call a physician.
Internal: Call a physician immediately. If swallowed, do not induce vomiting. Rinse mouth, then immediately drink one or two large glasses of water or milk. Never give anything by mouth to an unconscious person.
Inhalation of vapors: Should not occur with proper use of this product
Most important symptoms/effects, acute and delayed: None Known
Immediate medical attention and special treatment needed, if any: None Known
IMPORTANT:
Do not mix Perox-50™ with any other teat spray, teat dip or other teat products.
Perox-50™ is not intended to cure or help the healing of chapped or irritated teats.
In case of teat irritation or chapping, have the condition examined.
Keep from freezing. If frozen, let thaw and shake thoroughly before using.

DIRECTIONS:
Pre-dipping: Just prior to milking - Dip, spray or foam teat with undiluted Perox 50™. Cover to base of udder. Allow 15 – 30 seconds of contact time. Dry with a single service towel before attaching milking units. If using dip cups, replace solution if it becomes visibly dirty.
Post dipping: Immediately after milking - dip, spray or foam teat with undiluted Perox 50™. Cover to the base of the udder. Allow to air dry. If using dip cups, replace solution if it becomes visibly dirty. During cold weather, do not turn cows out until the teats are dry to prevent chapping and freezing. If necessary, wipe dry with single service towel.

FOR CHEMICAL EMERGENCIES
CALL CHEMTREC AT 800-424-9300